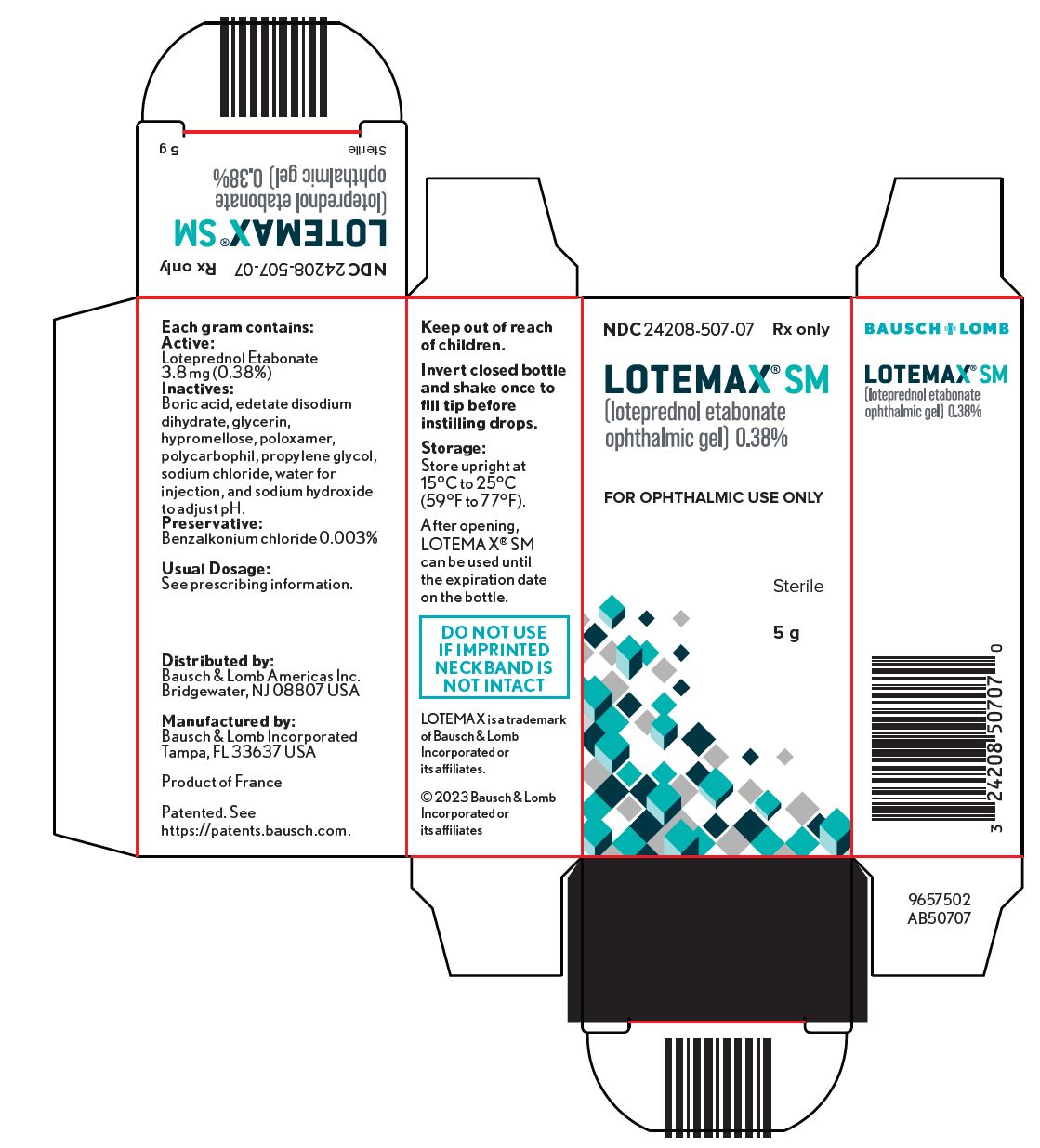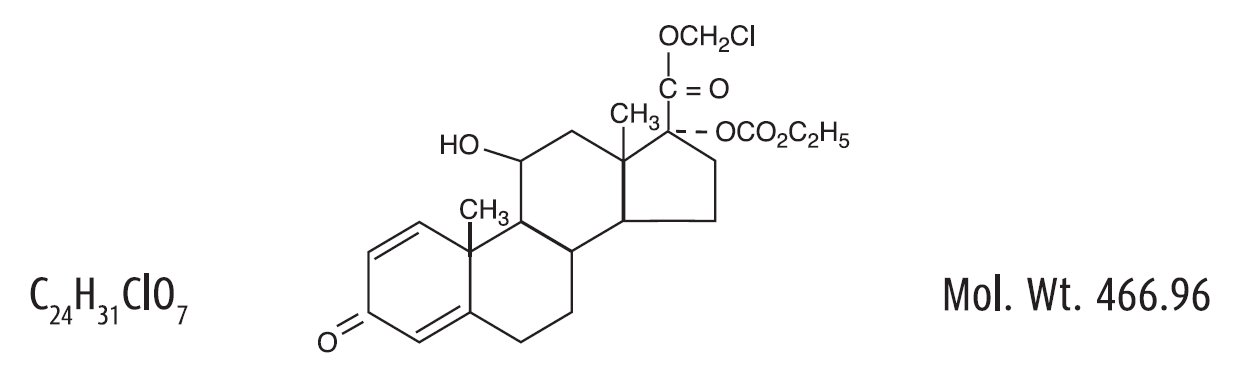 DRUG LABEL: Lotemax SM
NDC: 24208-507 | Form: GEL
Manufacturer: Bausch & Lomb Incorporated
Category: prescription | Type: HUMAN PRESCRIPTION DRUG LABEL
Date: 20230317

ACTIVE INGREDIENTS: LOTEPREDNOL ETABONATE 3.8 mg/1 g
INACTIVE INGREDIENTS: BORIC ACID; EDETATE DISODIUM; GLYCERIN; HYPROMELLOSE, UNSPECIFIED; POLOXAMER 407; POLYCARBOPHIL; PROPYLENE GLYCOL; SODIUM CHLORIDE; WATER; SODIUM HYDROXIDE; BENZALKONIUM CHLORIDE

HIGHLIGHTS OF PRESCRIBING INFORMATION

These highlights do not include all the information needed to use LOTEMAX® SM safely and effectively. See full prescribing information for LOTEMAX® SM.
LOTEMAX® SM (loteprednol etabonate ophthalmic gel), for topical ophthalmic use
Initial U.S. Approval: 1998

1 INDICATIONS AND USAGE

LOTEMAX® SM is a corticosteroid indicated for the treatment of post-operative inflammation and pain following ocular surgery. (1)

2 DOSAGE AND ADMINISTRATION

Invert closed bottle and shake once to fill tip before instilling drops. (2)

Apply one drop of LOTEMAX® SM into the conjunctival sac of the affected eye three times daily beginning the day after surgery and continuing throughout the first 2 weeks of the post-operative period. (2)

3 DOSAGE FORMS AND STRENGTHS

LOTEMAX® SM is a sterile preserved ophthalmic gel containing 3.8 mg of loteprednol etabonate per gram of gel. (3)

4 CONTRAINDICATIONS

LOTEMAX® SM, as with other ophthalmic corticosteroids, is contraindicated in most viral diseases of the cornea and conjunctiva including epithelial herpes simplex keratitis (dendritic keratitis), vaccinia, and varicella, and also in mycobacterial infection of the eye and fungal diseases of ocular structures. (4)

5 WARNINGS AND PRECAUTIONS

- Intraocular pressure (IOP) increase - Prolonged use of corticosteroids may result in glaucoma with damage to the optic nerve, defects in visual acuity and fields of vision. If this product is used for 10 days or longer, IOP should be monitored. (5.1)
- Cataracts - Use of corticosteroids may result in posterior subcapsular cataract formation. (5.2)
- Delayed healing – The use of steroids after cataract surgery may delay healing and increase the incidence of bleb formation. In those diseases causing thinning of the cornea or sclera, perforations have been known to occur with the use of topical steroids. The initial prescription and renewal of the medication order should be made by a physician only after examination of the patient with the aid of magnification such as slit lamp biomicroscopy and, where appropriate, fluorescein staining. (5.3)
- Bacterial infections – Prolonged use of corticosteroids may suppress the host response and thus increase the hazard of secondary ocular infections. In acute purulent conditions, steroids may mask infection or enhance existing infection. (5.4)
- Viral infections – Employment of a corticosteroid medication in the treatment of patients with a history of herpes simplex requires great caution. Use of ocular steroids may prolong the course and may exacerbate the severity of many viral infections of the eye (including herpes simplex). (5.5)
- Fungal infections – Fungal infections of the cornea are particularly prone to develop coincidentally with long-term local steroid application. Fungus invasion must be considered in any persistent corneal ulceration where a steroid has been used or is in use. (5.6)

6 ADVERSE REACTIONS

There were no treatment-emergent adverse drug reactions that occurred in more than 1% of subjects in the three times daily group compared to vehicle. (6)

To report SUSPECTED ADVERSE REACTIONS, contact Bausch & Lomb Incorporated at 1-800-553-5340 or FDA at 1-800-FDA-1088 or www.fda.gov/medwatch.

FULL PRESCRIBING INFORMATION

1 INDICATIONS AND USAGE

LOTEMAX® SM (loteprednol etabonate ophthalmic gel) 0.38% is a corticosteroid indicated for the treatment of post-operative inflammation and pain following ocular surgery.

2 DOSAGE AND ADMINISTRATION

Invert closed bottle and shake once to fill tip before instilling drops. Apply one drop of LOTEMAX® SM into the conjunctival sac of the affected eye three times daily beginning the day after surgery and continuing throughout the first 2 weeks of the post-operative period.

3 DOSAGE FORMS AND STRENGTHS

LOTEMAX® SM (loteprednol etabonate ophthalmic gel) 0.38% is a sterile preserved ophthalmic gel containing 3.8 mg of loteprednol etabonate per gram of gel.

4 CONTRAINDICATIONS

LOTEMAX® SM, as with other ophthalmic corticosteroids, is contraindicated in most viral diseases of the cornea and conjunctiva including epithelial herpes simplex keratitis (dendritic keratitis), vaccinia, and varicella, in mycobacterial infection of the eye and fungal diseases of ocular structures.

5 WARNINGS AND PRECAUTIONS

5.1 Intraocular Pressure (IOP) Increase

Prolonged use of corticosteroids may result in glaucoma with damage to the optic nerve, defects in visual acuity and fields of vision. Steroids should be used with caution in the presence of glaucoma. If this product is used for 10 days or longer, intraocular pressure should be monitored.

5.2 Cataracts

Use of corticosteroids may result in posterior subcapsular cataract formation.

5.3 Delayed Healing

The use of steroids after cataract surgery may delay healing and increase the incidence of bleb formation. In those diseases causing thinning of the cornea or sclera, perforations have been known to occur with the use of topical steroids. The initial prescription and renewal of the medication order should be made by a physician only after examination of the patient with the aid of magnification such as slit lamp biomicroscopy and, where appropriate, fluorescein staining.

5.4 Bacterial Infections

Prolonged use of corticosteroids may suppress the host response and thus increase the hazard of secondary ocular infections. In acute purulent conditions of the eye, steroids may mask infection or enhance existing infection.

5.5 Viral Infections

Employment of a corticosteroid medication in the treatment of patients with a history of herpes simplex requires great caution. Use of ocular steroids may prolong the course and may exacerbate the severity of many viral infections of the eye (including herpes simplex).

5.6 Fungal Infections

Fungal infections of the cornea are particularly prone to develop coincidentally with long-term local steroid application. Fungus invasion must be considered in any persistent corneal ulceration where a steroid has been used or is in use. Fungal cultures should be taken when appropriate.

5.7 Contact Lens Wear

Contact lenses should not be worn when the eyes are inflamed.

6 ADVERSE REACTIONS

Because clinical trials are conducted under widely varying conditions, adverse reaction rates observed in the clinical trials of a drug cannot be directly compared to rates in the clinical trials of another drug and may not reflect the rates observed in practice.

Adverse reactions associated with ophthalmic steroids include elevated intraocular pressure, which may be associated with infrequent optic nerve damage, visual acuity and field defects, posterior subcapsular cataract formation, delayed wound healing and secondary ocular infection from pathogens including herpes simplex, and perforation of the globe where there is thinning of the cornea or sclera.

There were no treatment-emergent adverse drug reactions that occurred in more than 1% of subjects in the three times daily group compared to vehicle.

8 USE IN SPECIFIC POPULATIONS

8.1 Pregnancy

Risk Summary

There are no adequate and well controlled studies with loteprednol etabonate in pregnant women.

Loteprednol etabonate produced teratogenicity at clinically relevant doses in the rabbit and rat when administered orally during pregnancy. Loteprednol etabonate produced malformations when administered orally to pregnant rabbits at doses 4.2 times the recommended human ophthalmic dose (RHOD) and to pregnant rats at doses 106 times the RHOD. In pregnant rats receiving oral doses of loteprednol etabonate during the period equivalent to the last trimester of pregnancy through lactation in humans, survival of offspring was reduced at doses 10.6 times the RHOD. Maternal toxicity was observed in rats at doses 1066 times the RHOD, and a maternal no observed adverse effect level (NOAEL) was established at 106 times the RHOD.

The background risk of major birth defects and miscarriage for the indicated population is unknown. However, the background risk in the U.S. general population of major birth defects is 2 to 4%, and of miscarriage is 15 to 20%, of clinically recognized pregnancies.

Data

Animal Data

Embryofetal studies were conducted in pregnant rabbits administered loteprednol etabonate by oral gavage on gestation days 6 to 18, to target the period of organogenesis. Loteprednol etabonate produced fetal malformations at 0.1 mg/kg (4.2 times the recommended human ophthalmic dose (RHOD) based on body surface area, assuming 100% absorption). Spina bifida (including meningocele) was observed at 0.1 mg/kg, and exencephaly and craniofacial malformations were observed at 0.4 mg/kg (17 times the RHOD). At 3 mg/kg (128 times the RHOD), loteprednol etabonate was associated with increased incidences of abnormal left common carotid artery, limb flexures, umbilical hernia, scoliosis, and delayed ossification. Abortion and embryofetal lethality (resorption) occurred at 6 mg/kg (256 times the RHOD). A NOAEL for developmental toxicity was not established in this study. The NOAEL for maternal toxicity in rabbits was 3 mg/kg/day.

Embryofetal studies were conducted in pregnant rats administered loteprednol etabonate by oral gavage on gestation days 6 to 15, to target the period of organogenesis. Loteprednol etabonate produced fetal malformations, including absent innominate artery at 5 mg/kg (106 times the RHOD); and cleft palate, agnathia, cardiovascular defects, umbilical hernia, decreased fetal body weight and decreased skeletal ossification at 50 mg/kg (1066 times the RHOD). Embryofetal lethality (resorption) was observed at 100 mg/kg (2133 times the RHOD). The NOAEL for developmental toxicity in rats was 0.5 mg/kg (10.6 times the RHOD). Loteprednol etabonate was maternally toxic (reduced body weight gain) at 50 mg/kg/day. The NOAEL for maternal toxicity was 5 mg/kg.

A peri-/postnatal study was conducted in rats administered loteprednol etabonate by oral gavage from gestation day 15 (start of fetal period) to postnatal day 21 (the end of lactation period). At 0.5 mg/kg (10.6 times the clinical dose), reduced survival was observed in live-born offspring. Doses ≥ 5 mg/kg (106 times the RHOD) caused umbilical hernia/incomplete gastrointestinal tract. Doses ≥ 50 mg/kg (1066 times the RHOD) produced maternal toxicity (reduced body weight gain, death), decreased number of live-born offspring, decreased birth weight, and delays in postnatal development. A developmental NOAEL was not established in this study. The NOAEL for maternal toxicity was 5 mg/kg.

8.2 Lactation

There are no data on the presence of loteprednol etabonate in human milk, the effects on the breastfed infant, or the effects on milk production. The developmental and health benefits of breastfeeding should be considered, along with the mother’s clinical need for LOTEMAX® SM and any potential adverse effects on the breastfed infant from LOTEMAX® SM.

8.4 Pediatric Use

Safety and effectiveness of LOTEMAX® SM in pediatric patients have not been established.

8.5 Geriatric Use

No overall differences in safety and effectiveness have been observed between elderly and younger patients.

11 DESCRIPTION

LOTEMAX® SM (loteprednol etabonate ophthalmic gel) 0.38% contains a sterile, topical corticosteroid for ophthalmic use. Loteprednol etabonate is a white to off-white powder.

Loteprednol etabonate is represented by the following structural formula:

Chemical Name:

chloromethyl 17α-[(ethoxycarbonyl)oxy]-11β-hydroxy-3-oxoandrosta-1,4-diene-17β-carboxylate

Each gram contains:

- Active: loteprednol etabonate 3.8 mg (0.38%);
- Inactives: boric acid, edetate disodium dihydrate, glycerin, hypromellose, poloxamer, polycarbophil, propylene glycol, sodium chloride, water for injection, and sodium hydroxide to adjust to a pH of between 6 and 7.
- Preservative: benzalkonium chloride 0.003%

12 CLINICAL PHARMACOLOGY

12.1 Mechanism of Action

Loteprednol etabonate is a corticosteroid. Corticosteroids have been shown to inhibit the inflammatory response to a variety of inciting agents. They inhibit the edema, fibrin deposition, capillary dilation, leukocyte migration, capillary proliferation, fibroblast proliferation, deposition of collagen, and scar formation associated with inflammation. While glucocorticoids are known to bind to and activate the glucocorticoid receptor, the molecular mechanisms involved in glucocorticoid/glucocorticoid receptor-dependent modulation of inflammation are not clearly established. However, corticosteroids are thought to inhibit prostaglandin production through several independent mechanisms.

12.3 Pharmacokinetics

The pharmacokinetic exposure to loteprednol etabonate following topical bilateral ocular administration of one drop three times daily of LOTEMAX® SM for up to two weeks (Day 15) was evaluated in 18 healthy adult subjects. Plasma concentrations of loteprednol etabonate were analyzed using a validated LC/MS/MS method and the lower limit of quantitation for loteprednol etabonate was 0.05 ng/mL. The mean (± SD) Cmax values for loteprednol etabonate in plasma were 0.13 (± 0.06) ng/mL on Day 1 after a single dose and 0.16 (± 0.06) ng/mL after the last dose on Day 15 of the study. The mean (± SD) AUCt values for loteprednol etabonate in plasma were 0.15 (± 0.15) hr•ng/mL on Day 1 after a single dose and 0.35 (± 0.32) hr•ng/mL after the last dose on Day 15.

13 NONCLINICAL TOXICOLOGY

13.1 Carcinogenesis, Mutagenesis, Impairment of Fertility

Long-term animal studies have not been conducted to evaluate the carcinogenic potential of loteprednol etabonate. Loteprednol etabonate was not genotoxic in vitroin the Ames test, the mouse lymphoma tk assay, or in the chromosomal aberration test in human lymphocytes, or in vivoin the mouse micronucleus assay. Treatment of male and female rats with 25 mg/kg/day of loteprednol etabonate (533 times the RHOD based on body surface area, assuming 100% absorption) prior to and during mating caused preimplantation loss and decreased the number of live fetuses/live births. The NOAEL for fertility in rats was 5 mg/kg/day (106 times the RHOD).

14 CLINICAL STUDIES

In two randomized, multicenter, double-masked, parallel group, vehicle-controlled trials in patients who underwent cataract extraction with intraocular lens implantation, LOTEMAX® SM administered three times daily to the affected eye beginning the day after cataract surgery was more effective compared to its vehicle in resolving anterior chamber inflammation and pain following surgery. In these studies, LOTEMAX® SM had statistically significantly higher rates of subjects with complete clearing of anterior chamber cells and of subjects who were pain free at post-operative Day 8 compared to vehicle. Results are shown in the following table.

Proportion of Subjects with Complete Clearing of Anterior Chamber Cells and Proportion of Subjects with Complete Resolution of Pain at Post-Operative Day 8.
Outcome | Study 1 |  |  | Study 2
Outcome | LOTEMAX® SM N=171 n (%) | Vehicle N=172 n (%) | Difference (95 CI) % | LOTEMAX® SM N=200 n (%) | Vehicle N=199 n (%) | Difference (95% CI) %
Cells | 49; (29%) | 16; (9%) | 19 (11, 27) | 61; (31%) | 40; (20%) | 10 (2, 19)
Pain | 125; (73%) | 82; (48%) | 25 (15, 35) | 151; (76%) | 99; (50%) | 26 (17, 35)

16 HOW SUPPLIED/STORAGE AND HANDLING

LOTEMAX® SM (loteprednol etabonate ophthalmic gel) 0.38% is a sterile ophthalmic submicron gel supplied in a white low-density polyethylene plastic bottle with a white controlled drop tip and a pink polypropylene cap in the following size:

NDC 24208-507-07 5g in a 10 mL bottle

Use only if imprinted neckband is intact.

Storage: Store upright at 15ºC to 25ºC (59ºF to 77ºF). After opening, LOTEMAX® SM can be used until the expiration date on the bottle.

17 PATIENT COUNSELING INFORMATION

Administration

Invert closed bottle and shake once to fill tip before instilling drops.

Risk of Contamination

Advise patients not to allow the dropper tip to touch any surface, as this may contaminate the gel.

Contact Lens Wear

Advise patients contact lenses should not be worn when the eyes are inflamed.

Risk of Secondary Infection

Advise the patient to consult a physician if pain develops, redness, itching or inflammation becomes aggravated.

Distributed by:

Bausch & Lomb Americas Inc.

Bridgewater, NJ 08807 USA

Manufactured by:

Bausch & Lomb Incorporated

Tampa, FL 33637 USA

Patented. See https://patents.bausch.com.

LOTEMAX is a trademark of Bausch & Lomb Incorporated or its affiliates.

© 2023 Bausch & Lomb Incorporated or its affiliates

9669602 (Folded)

9669702 (Flat)

PACKAGE/LABEL PRINCIPAL DISPLAY PANEL

NDC 24208-507-07

Rx only

Lotemax® SM

(loteprednol etabonate

Ophthalmic gel) 0.38%

FOR OPHTHALMIC USE ONLY

Sterile

5 g